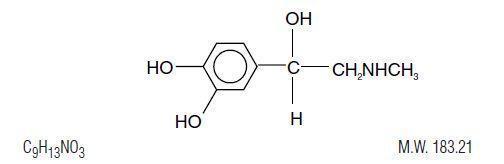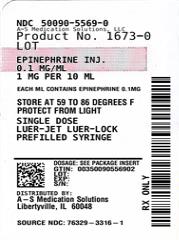 DRUG LABEL: 
                  Epinephrine 
                
NDC: 50090-5569 | Form: INJECTION
Manufacturer: A-S Medication Solutions
Category: prescription | Type: HUMAN PRESCRIPTION DRUG LABEL
Date: 20221004

ACTIVE INGREDIENTS: EPINEPHRINE 0.1 mg/1 mL
INACTIVE INGREDIENTS: SODIUM BISULFITE; SODIUM CHLORIDE; HYDROCHLORIC ACID; SODIUM CITRATE, UNSPECIFIED FORM; CITRIC ACID MONOHYDRATE

EPINEPHRINE INJECTION, USP

AVAILABLE AS:
EPINEPHRINE INJECTION, USP, 0.1 mg/mL
FOR INTRACARDIAC OR
INTRAVENOUS USE

DESCRIPTION

Epinephrine is the active principle of the adrenal medulla. Chemically described as (-)-3,4-Dihydroxy-α-[(methyl-amino) methyl] benzyl alcohol, it has the following structural formula:

Epinephrine is a sterile aqueous solution of epinephrine prepared with the aid of hydrochloric acid. Each mL of the solution contains 0.1 mg epinephrine and 1 mg sodium bisulfite. Sodium bisulfite is an antioxidant. This solution also contains sodium chloride for adjustment of tonicity, and 10% w/v hydrochloric acid to dissolve epinephrine and to adjust pH to meet USP limits of 2.2 to 5.0. Additionally, the solution also contains sodium citrate and citric acid as buffers for stabilization. The air above the liquid in the individual containers have been displaced by flushing with nitrogen during the filling operation. No antimicrobial preservatives have been added and each vial is intended as a single dose; once the unit is assembled and used, any remaining portion of the solution must be discarded with the entire unit.

CLINICAL PHARMACOLOGY

The actions of epinephrine resemble the effects of stimulation of adrenergic nerves. To a variable degree, it acts on both alpha and beta receptor sites of sympathetic effector cells. Its most prominent actions are on the beta receptors of the heart, vascular and other smooth muscle. When given by rapid I.V. injection it produces a rapid rise in blood pressure, mainly systolic, direct stimulation of cardiac muscle which increases the strength of ventricular contraction, increases the heart rate, and constricts the arterioles in the skin, mucosa and splanchnic areas of circulation.

Epinephrine relaxes the smooth muscle of the bronchi and iris and is a physiologic antagonist of histamine.

The drug also produces an increase in blood sugar and glycogenolysis in the liver.

Blood pressure: When given by slow I.V. injection, epinephrine usually produces a moderate rise in systolic and a fall in diastolic pressure. Although some increase in pulse pressure occurs, there is usually no great elevation in mean blood pressure. Accordingly, the compensatory reflex mechanisms that cause a pronounced increase in blood pressure do not antagonize the direct cardiac actions of epinephrine as much as with catecholamines that have a predominant action on alpha receptors.

Total peripheral resistance: By action of epinephrine on beta receptors of the skeletal muscle vasculature, total peripheral resistance decreases, and blood flow is thereby enhanced. Usually, this vasodilator effect predominates so that the modest rise in systolic pressure which follows slow injection or absorption is the result of direct cardiac stimulation and increase in cardiac output. In some instances, peripheral resistance is not altered or may even rise, owing to a greater ratio of alpha to beta activity in different vascular areas.

Pharmacokinetics: Intravenous injection produces an immediate and intensified response. Following I.V. injection, epinephrine disappears rapidly from the blood stream. Subcutaneously or I.M. administered epinephrine has a rapid onset and short duration of action. Subcutaneous administration during asthmatic attacks may produce bronchodilation within 5 to 10 minutes, and maximal effects may occur within 20 minutes.

The drug becomes fixed in the tissues and is rapidly inactivated chiefly by enzymic transformation to metanephrine or normetanephrine, either of which is subsequently conjugated and excreted in the urine in the form of sulfates and glucuronides. Either sequence results in the formation of 3-methoxy-4-hydroxy-mandelic acid (vanillylmandelic acid, VMA) which is also detectable in the urine.

INDICATIONS AND USAGE

EPINEPHRINE

Epinephrine’s cardiac effects may be of use in the treatment and prophylaxis of cardiac arrest due to various causes in the absence of ventricular fibrillation and attacks of transitory atrioventricular (AV) heart block with syncopal seizures (Stokes-Adams syndrome), but it is not used in cardiac failure or in hemorrhagic, traumatic or in cardiogenic shock. Epinephrine may be used to stimulate the heart in syncope due to complete heart block or carotid sinus hypersensitivity. Epinephrine is also used for resuscitation in cardiac arrest following anesthetic accidents. In cardiopulmonary resuscitation, intracardiac puncture and intramyocardial injection of epinephrine may be effective when external cardiac compression and attempts to restore the circulation by electrical defibillation or use of a pacemaker fail. Epinephrine is seldom used as a vasopressor except in the treatment of anaphylactic shock and under certain conditions in insulin shock.

CONTRAINDICATIONS

Epinephrine should not be used in the presence of cardiac dilatation or coronary insufficiency.

Epinephrine is contraindicated in shock during general anesthesia with halogenated hydrocarbons or cyclopropane, and in individuals with organic brain damage. Epinephrine is also contraindicated with local anesthesia of certain areas; e.g., fingers, toes, because of the danger of vasoconstriction producing sloughing of tissue; also contraindicated in labor because it may delay the second stage.

Epinephrine should not be used in those cases where vasopressor drugs may be contraindicated, e.g., in thyrotoxicosis, diabetes, in obstetrics when maternal blood pressure is in excess of 130/80, and in hypertension and other cardiovascular disorders.

WARNINGS

EPINEPHRINE

Contains sodium bisulfite, a sulfite that may cause allergic-type reactions including anaphylactic symptoms and life-threatening or less severe asthmatic episodes in certain susceptible people. The overall prevalence of sulfite sensitivity in the general population is unknown and probably low. Sulfite sensitivity is seen more frequently in asthmatic rather than in non-asthmatic people.

Use with caution in the following: Elderly; those with cardiovascular disease, hypertension, diabetes, or hyperthyroidism; in psychoneurotic individuals; bronchial asthma and emphysema with degenerative heart disease.

Cardiovascular effects: Inadvertently induced high arterial blood pressure may result in angina pectoris (especially when coronary insufficiency is present), or aortic rupture.

Epinephrine may induce potentially serious cardiac arrhythmias in patients not suffering from heart disease and patients with organic heart disease or who are receiving drugs that sensitize the myocardium. With Epinephrine, a paradoxical but transient lowering of blood pressure, bradycardia and apnea may occur immediately after injection.

Cerebrovascular hemorrhage: Overdosage or inadvertent I.V. injection of epinephrine may cause cerebrovascular hemorrhage resulting from the sharp rise in the blood pressure.

Pulmonary edema: Fatalities may also result from pulmonary edema because of the peripheral constriction and cardiac stimulation produced.

PRECAUTIONS

Although epinephrine can produce ventricular fibrillation, its actions in restoring electrical activity in asystole and in enhancing defibrillation are well documented. However, it should be used with caution in patients with ventricular fibrillation.

In patients with prefibrillatory rhythm, I.V. epinephrine must be used with extreme caution because of its excitatory action on the heart. Since the myocardium is sensitized to the drug by many anesthetic agents, epinephrine may convert asystole to ventricular fibrillation if used in the treatment of anesthetic cardiac accidents.

Hypovolemia: Use is not a substitute for the replacement of blood, plasma, fluids, and electrolytes, which should be restored promptly when loss has occurred.

DRUG INTERACTIONS

Drug interactions: Epinephrine must not be administered concomitantly with other sympathomimetic drugs (such as isoproterenol) because of possible additive effects and increased toxicity. Combined effects may induce serious cardiac arrhythmias. They may be administered alternately when the preceding effect of other such drugs has subsided.

Epinephrine is readily destroyed by alkalies and oxidizing agents (e.g., oxygen, chlorine, bromine, iodine, permanganates, chromates, nitrites, and salts of easily reducible metals, especially iron).

The effects of epinephrine may be potentiated by tricyclic antidepressants, certain antihistamines (e.g., diphenhydramine, tripelennamine, chlorpheniramine) and sodium I-thyroxine.

In obstetrics, if vasopressor drugs are used either to correct hypotension or added to the local anesthetic solution, some oxytocic drugs may cause severe persistent hypertension; even rupture of a cerebral blood vessel may occur during the postpartum period.

All vasopressors should be used cautiously in patients taking monoamine oxidase (MAO) inhibitors.

Cyclopropane or halogenated hydrocarbon anesthetics such as halothane which sensitize the myocardium may induce cardiac arrhythmia. (See Contraindications.) When encountered, such arrhythmias may respond to administration of a beta-adrenergic blocking drug.

Diruretic agents may decrease vascular response to pressor drugs such as epinephrine.

Epinephrine may antagonize the neuron blockade produced by guanethidine resulting in decreased antihypertensive effect and requiring increased dosage of the latter.

Use of epinephrine with excessive doses of digitalis, mercurial diuretics or other drugs that sensitize the heart to arrhythmias is not recommended.

Rapidly acting vasodilators such as nitrites or alpha-blocking agents may counteract the marked pressor effects of epinephrine.

Propranolol administered concomitantly with epinephrine may block the beta-adrenergic effects of epinephrine, causing hypertension.

Usage in Pregnancy: Teratogenic Effects - Pregnancy Category C
Epinephrine is teratogenic in small animals when given in doses about 25 times the human dose. There are no adequate and well controlled studies in pregnant women. Use during pregnancy only if the potential benefit justifies the potential risk to the fetus.

Usage in Labor and Delivery: Parenteral administration of epinephrine, if used to support blood pressure during low or other spinal anesthesia for delivery, can cause acceleration of fetal heart rate and should not be used in obstetrics when maternal blood pressure exceeds 130/80.

Usage in Children: Epinephrine should be administered with caution to infants and children. Syncope has occurred following the administration of epinephrine to asthmatic children.

ADVERSE REACTIONS

Transient and minor: Anxiety, headache, fear, and palpitations often occur with therapeutic doses, especially in hyperthyroid and hypertensive individuals.

Cardiac arrhythmias and excessive rise in blood pressure may occur with therapeutic doses or inadvertent overdosage.

Local: Repeated local injections can result in necrosis at sites of injection from vascular constriction.

Systemic: Cerebral hemorrhage; hemiplegia; subarachnoid hemorrhage; anginal pain in patients with angina pectoris; anxiety; restlessness; throbbing headache; tremor; weakness; dizziness; pallor; respiratory difficulty; palpitation; apprehensiveness; sweating; nausea; vomiting. “Epinephrine-fastness” can occur with prolonged use.

OVERDOSAGE

Symptoms: Erroneous administration of large doses of epinephrine may lead to precordial distress, vomiting, headache, dyspnea, as well as unusually elevated blood pressure.

Treatment: Most toxic effects can be counteracted by injection of an alpha-adrenergic blocker and a beta-adrenergic blocker. In the event of a sharp rise in blood pressure, rapid acting vasodilators such as the nitrites, or alpha-adrenergic blocking agents can counteract the marked pressor effects. If prolonged hypotension follows, it may be necessary to administer another pressor drug, such as norepinephrine.

If an epinephrine overdose induces pulmonary edema that interferes with respiration, treatment consists of a rapidly acting alpha-adrenergic blocking drug such as phentolamine and/or intermittent positive pressure respiration.

Treatment of cardiac arrhythmias consists of a beta-adrenergic blocking drug such as propranolol.

Epinephrine overdosage can also cause transient bradycardia followed by tachycardia; these may be accompanied by potentially fatal cardiac arrhythmias. Ventricular premature contractions may appear within one minute after injection and may be followed by multifocal ventricular tachycardia (prefibrillation rhythm). Subsidence of the ventricular effects may be followed by atrial tachycardia, and occasionally, by atrioventricular block.

Overdosage sometimes results in extreme pallor and coldness of the skin, metabolic acidosis and kidney failure. Take suitable corrective measures.

DOSAGE AND ADMINISTRATION

EPINEPHRINE

As Cardiac Stimulant:
Intravenous or Intracardiac Injection
Administer by I.V. injection and/or in cardiac arrest, by intracardiac injection into the left ventricular chamber. Intracardiac injection should only be administered by personnel well trained in the technique, if there has not been sufficient time to establish an intravenous route.

Adult Dosage: 1-10 mL (0.1 - 1 mg of epinephrine), repeated every five minutes, if necessary.

Pediatric Dosage: 0.05 - 0.1 mL/ kg of body weight (0.005 - 0.01 mg/ kg) e.g., 2 kg infant would receive 0.1 - 0.2 mL of epinephrine.

NOTE: Do not inject if fibrillation is occurring.

As Vasopressor (Anaphylaxis):
Intravenous Injection

Adult Dosage: 1-2.5 mL (0.1 - 0.25 mg of epinephrine), administered slowly. May be repeated every 5 to 15 minutes as needed.

Pediatric Dosage: 3 mL (0.3 mg of epinephrine), repeated every 15 minutes for 3 or 4 doses, if necessary.

NOTE: Parenteral drug products should be inspected visually for particulate matter and discoloration prior to administration, whenever solution and container permit.

HOW SUPPLIED

Product: 50090-5569

NDC: 50090-5569-0 10 mL in a VIAL / 10 in a PACKAGE

INTERNATIONAL MEDICATION SYSTEMS, LIMITED REV 3-16

SO. EL MONTE, CA 91733, U.S.A.
An Amphastar Pharmaceuticals Company

© INTERNATIONAL MEDICATION SYSTEMS, LIMITED 2016

6933160D